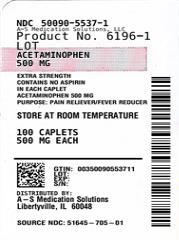 DRUG LABEL: PlusPharma Extra Strength
NDC: 50090-5537 | Form: TABLET
Manufacturer: A-S Medication Solutions
Category: otc | Type: HUMAN OTC DRUG LABEL
Date: 20210915

ACTIVE INGREDIENTS: ACETAMINOPHEN 500 mg/1 1
INACTIVE INGREDIENTS: POVIDONE, UNSPECIFIED; STARCH, CORN; SODIUM STARCH GLYCOLATE TYPE A CORN; STEARIC ACID

Acetaminophen 500 mg Caplet

DO NOT USE IF IMPRINTED SAFETY SEAL UNDER CAP IS BROKEN OR MISSING
Drug Facts

Active ingredient (in each caplet)

Acetaminophen 500 mg

Purposes
Pain reliever/fever reducer

Uses

- temporarily relieves minor aches and pains due to:
- headache
- muscular aches
- backache
- minor pain of arthritis
- the common cold
- toothache
- premenstrual and menstrual cramps
- temporarily reduces fever

Warnings

Liver warning: This product contains acetaminophen. Severe liver damage may occur if you take

- more than 4,000 mg of acetaminophen in 24 hours
- with other drugs containing acetaminophen
- 3 or more alcoholic drinks every day while using this product

Allergy alert: acetaminophen may cause severe skin reactions. Symptoms may include:

- skin reddening
- blisters
- rash

If a skin reaction occurs, stop use and seek medical help right away.

Do not use

- with any other drug containing acetaminophen (prescription or non prescription). If you are not sure whether a drug contains acetaminophen, ask a doctor or pharmacist.
- if you are allergic to acetaminophen or any of the inactive ingredients in this product

Ask a doctor before use if you have liver disease.

Ask a doctor or pharmacist before use if you are taking the blood thinning drug warfarin.

Stop use and ask a doctor if

- pain gets worse or lasts more than 10 days
- fever gets worse or lasts more than 3 days
- new symptoms occur
- redness or swelling is present

These could be signs of a serious condition.

PREGNANCY OR BREAST FEEDING

If pregnant or breast-feeding, ask a health professional before use.

Keep out of reach of children.

Overdose warning: In the case of overdose, get medical help or contact a Poison Control Center right away (1-800-222-1222). Quick medical attention is critical for adults as well as for children even if you do not notice any signs or symptoms.

Directions

- do not take more than directed (see overdose warning)
- adults and children 12 years and over:
- take 2 caplets every 6 hours while symptoms last
- do not take more than 6 caplets in 24 hours unless directed by a doctor
- do not take for more than 10 days unless directed by a doctor
- children under 12 years: ask a doctor

Other information

- store at room temperature in a dry place

INACTIVE INGREDIENT

Inactive ingredients Povidone, pregelatinized starch, sodium starch glycolate, stearic acid

QUESTIONS

Questions? If you have any questions or comments, or to report an adverse event, please contact (800) 795-9775.

Distributed By: Plus Pharma, Commack, NY 11725

Manufactured in a GMP facility in the USA

HOW SUPPLIED

Product: 50090-5537

NDC: 50090-5537-1 100 TABLET in a BOTTLE, PLASTIC